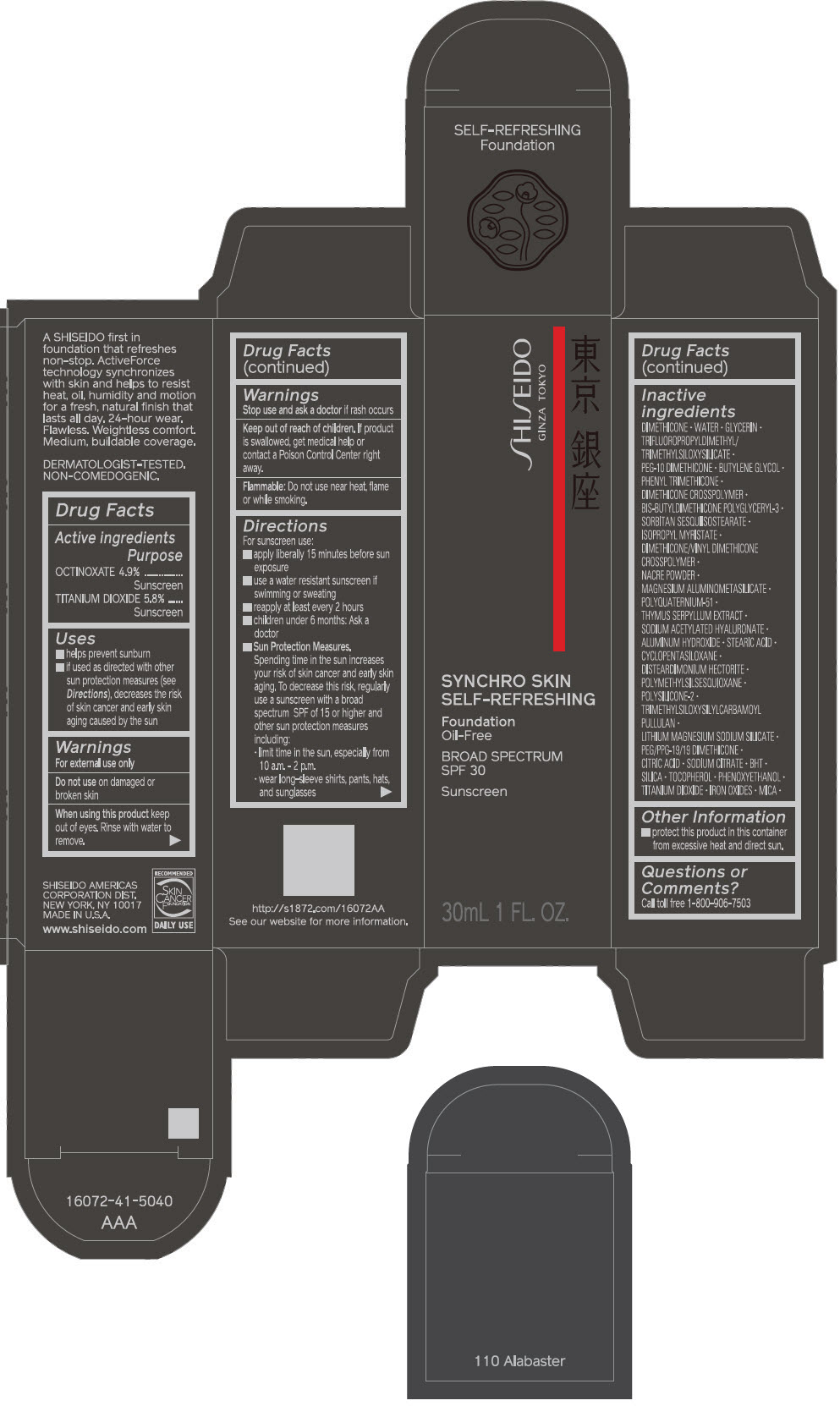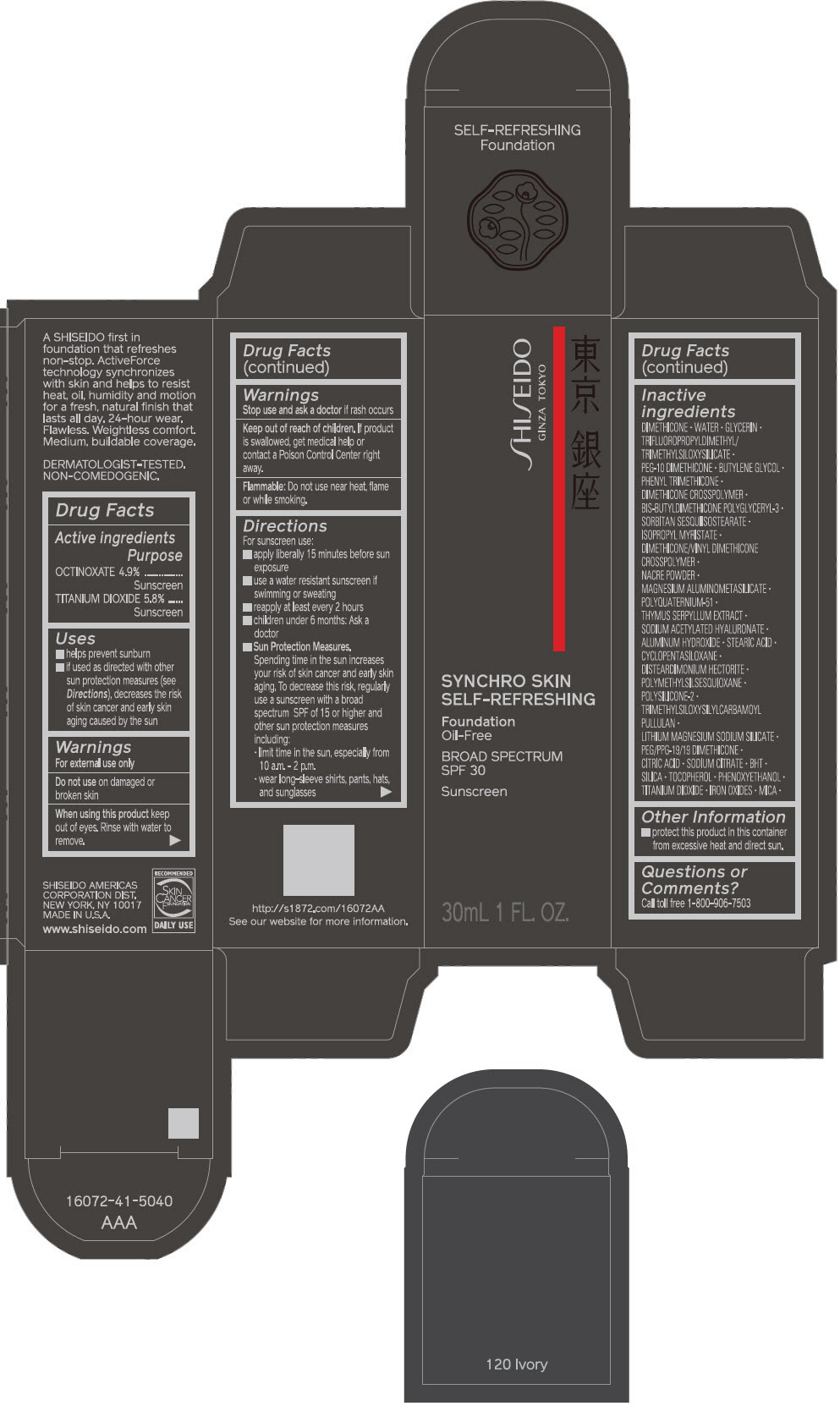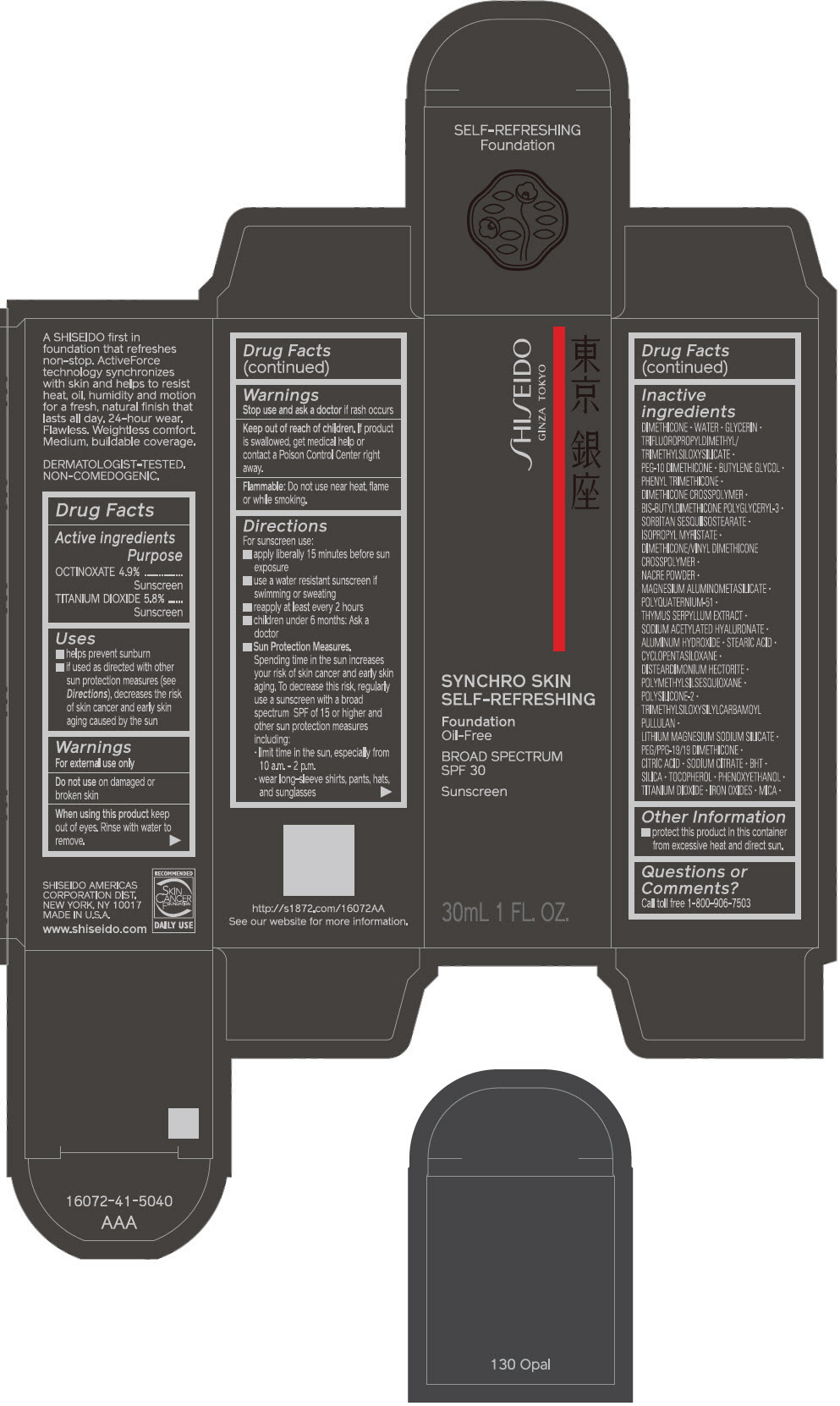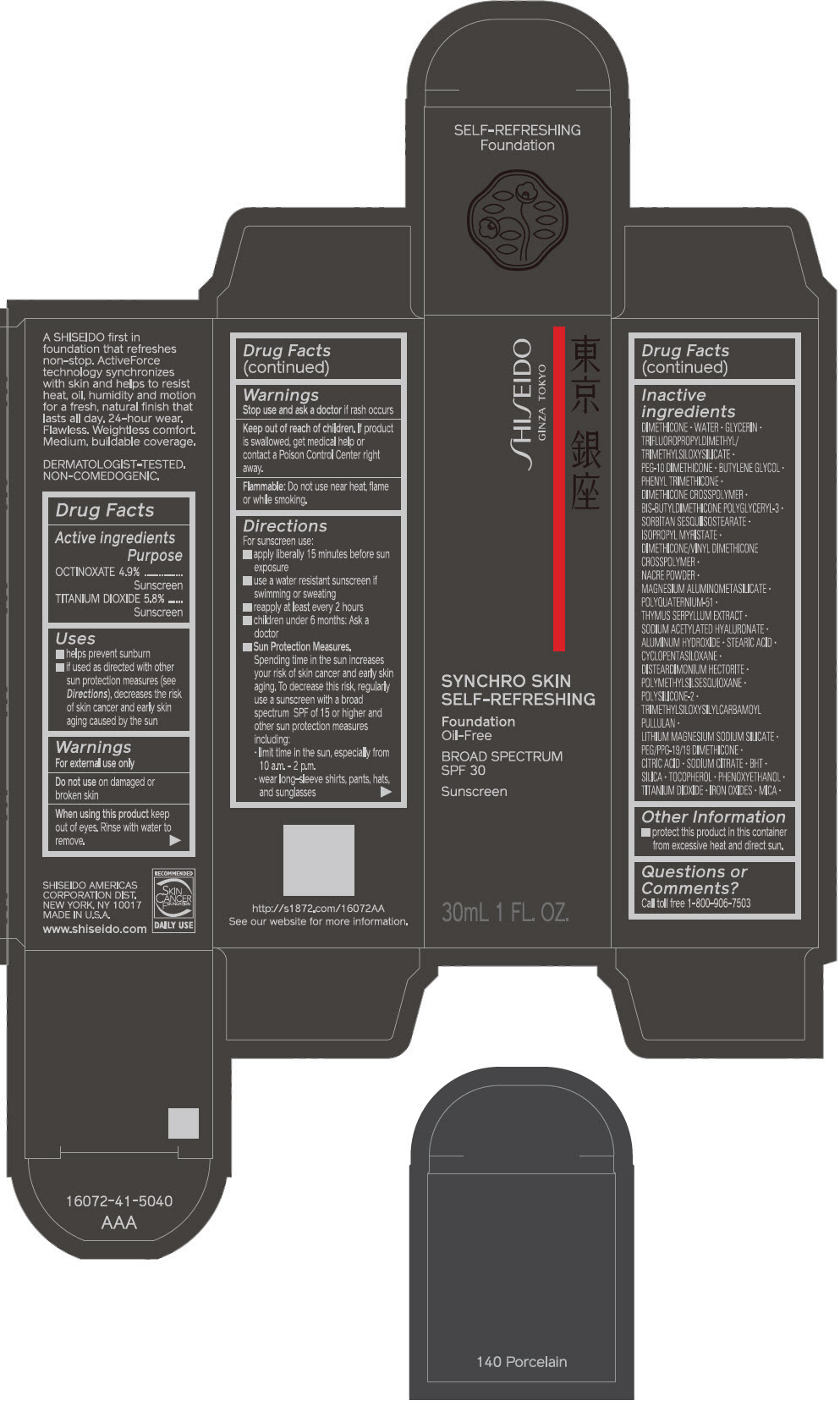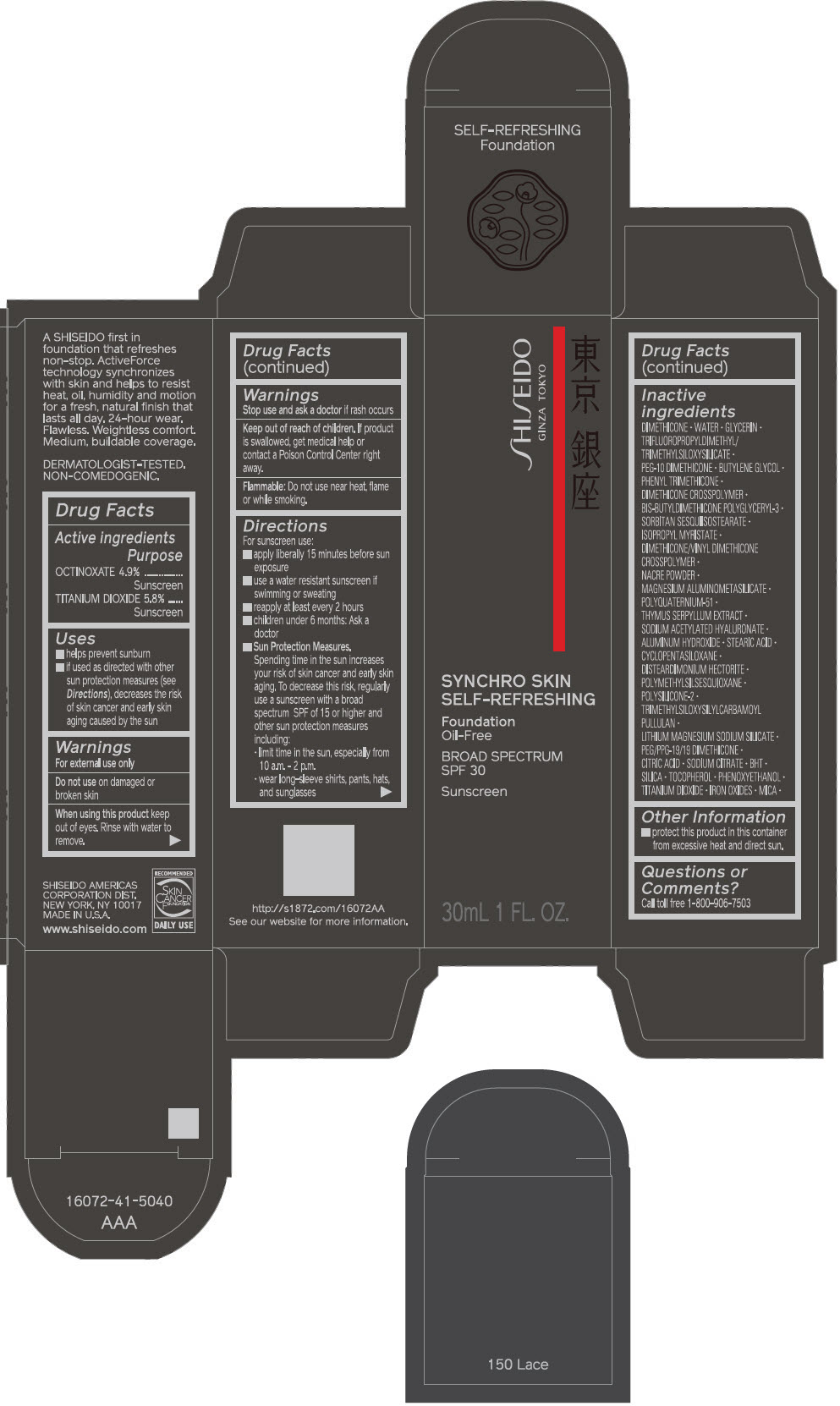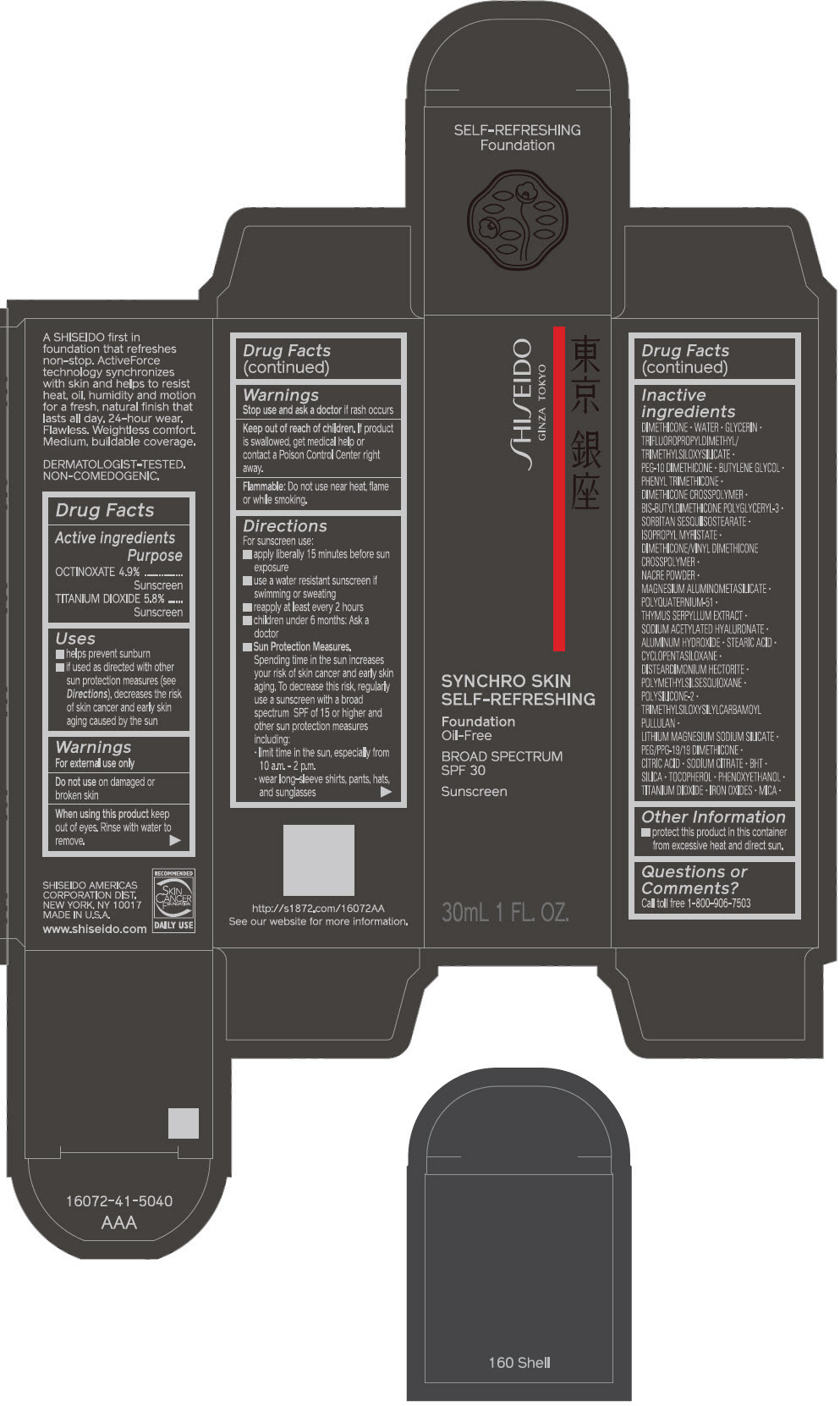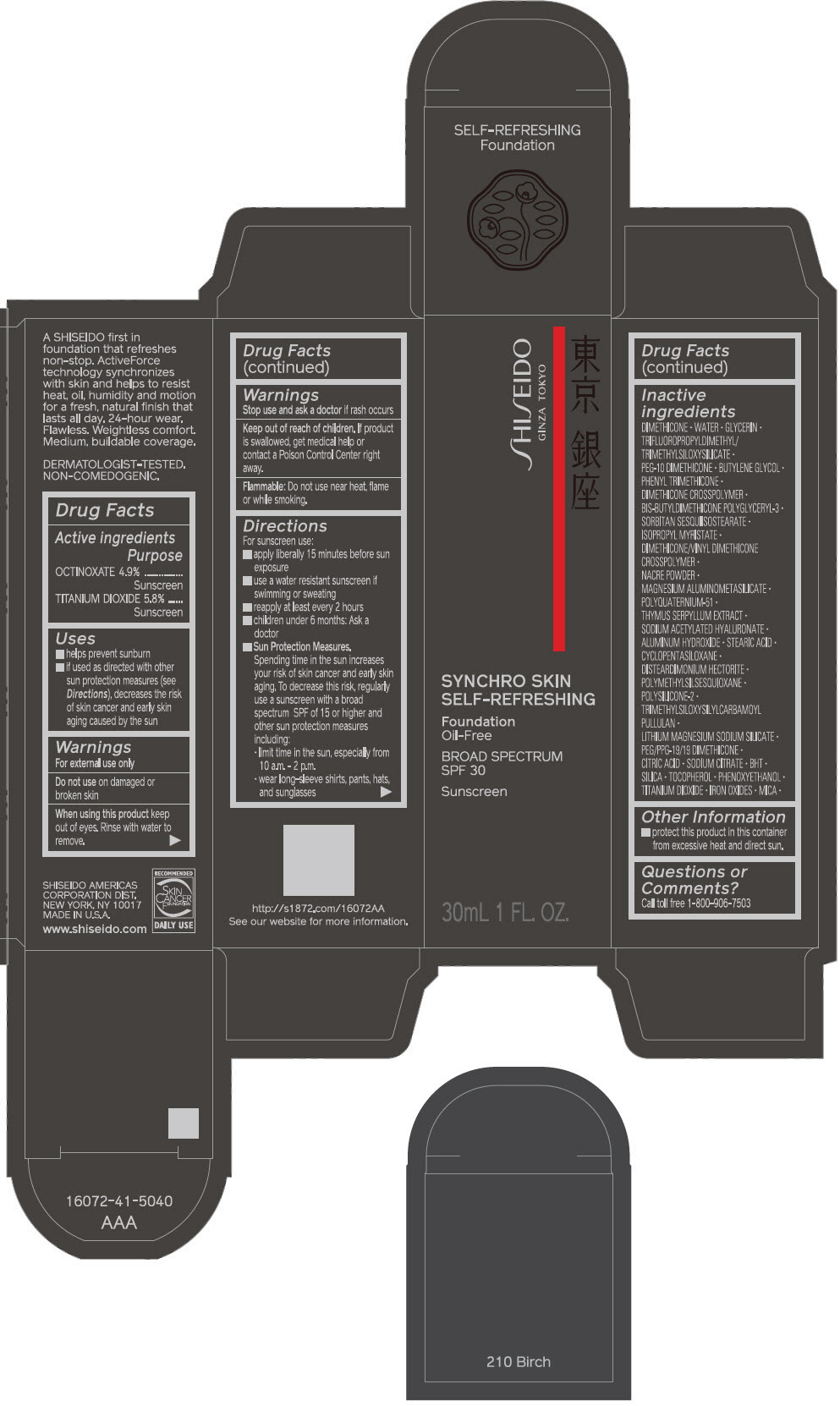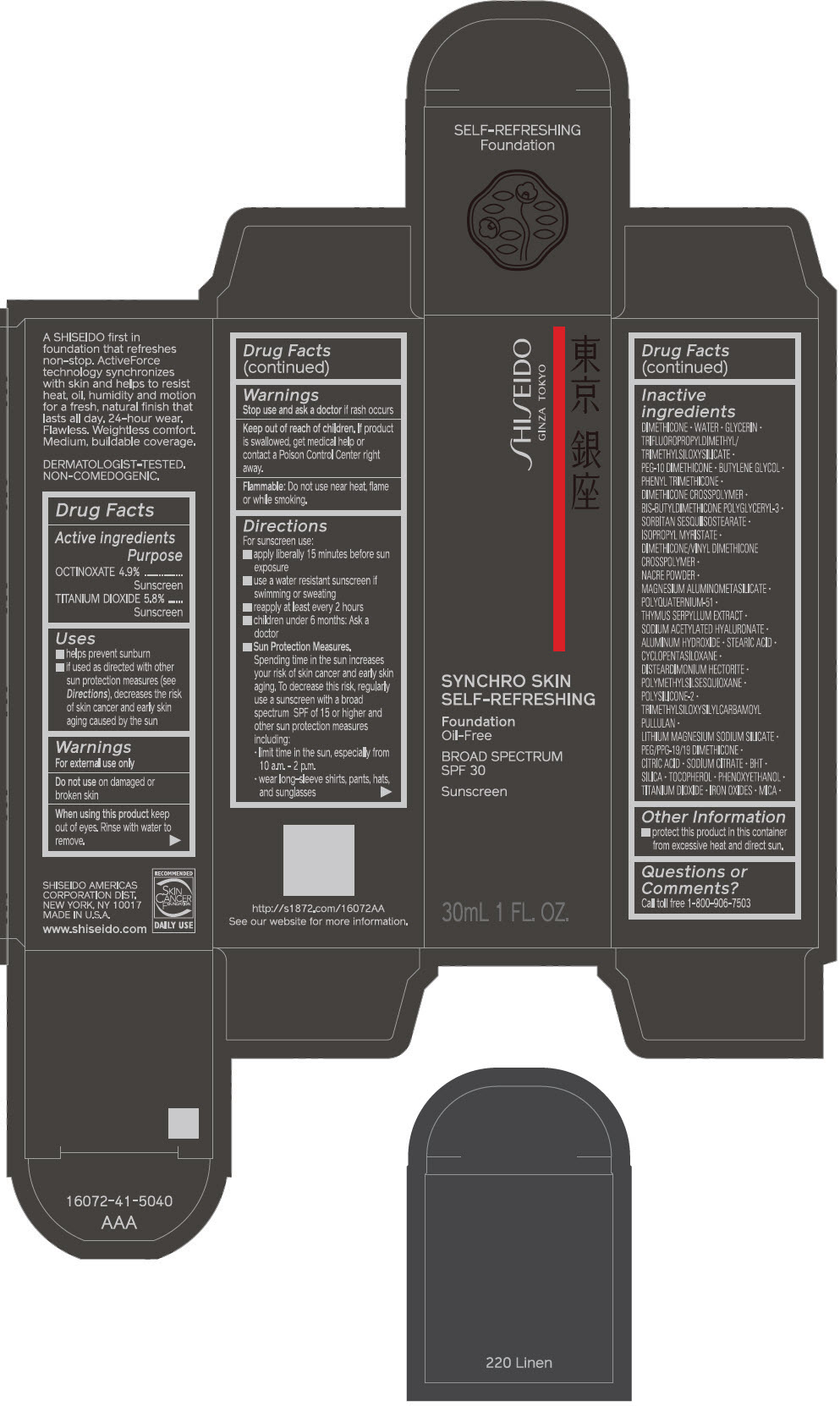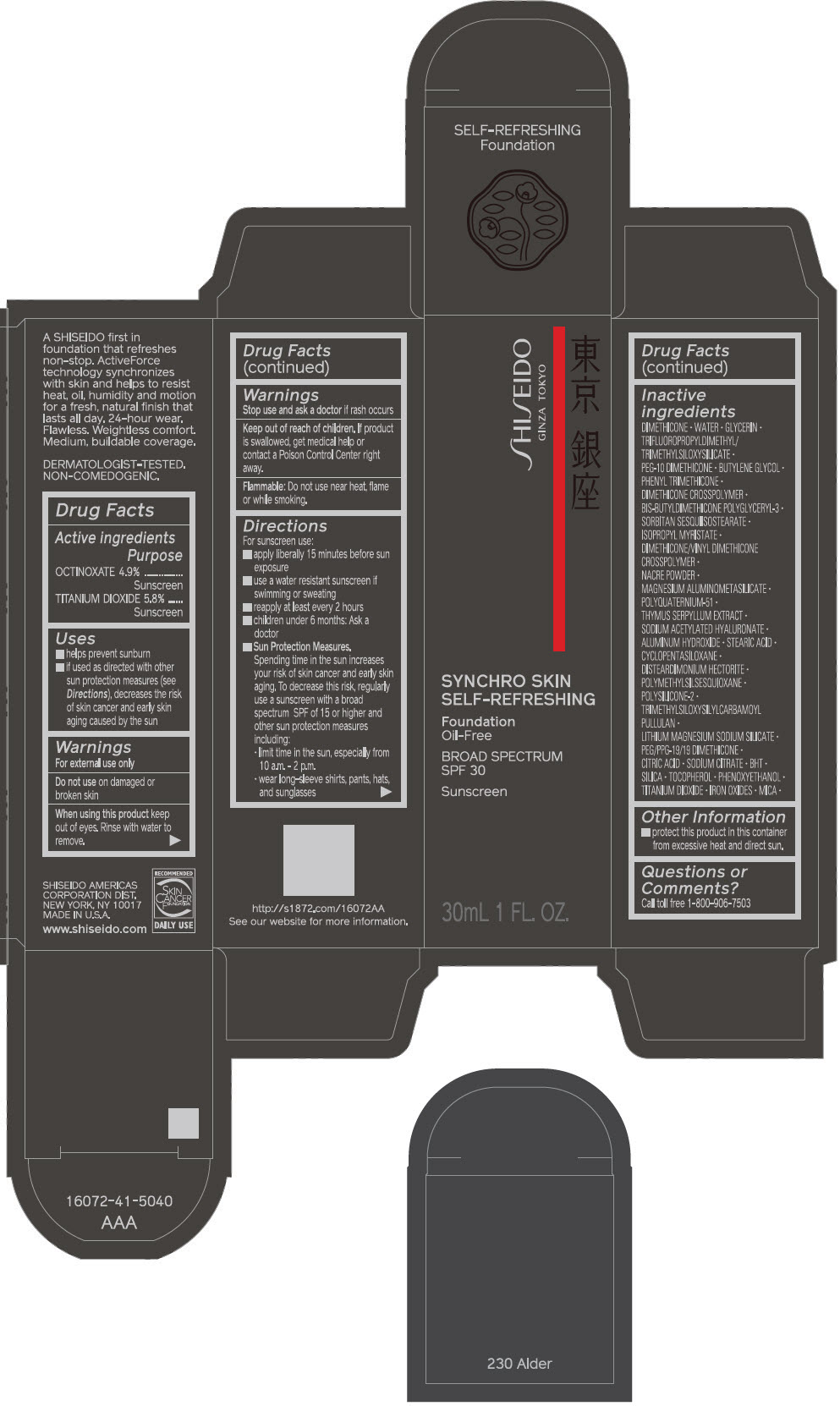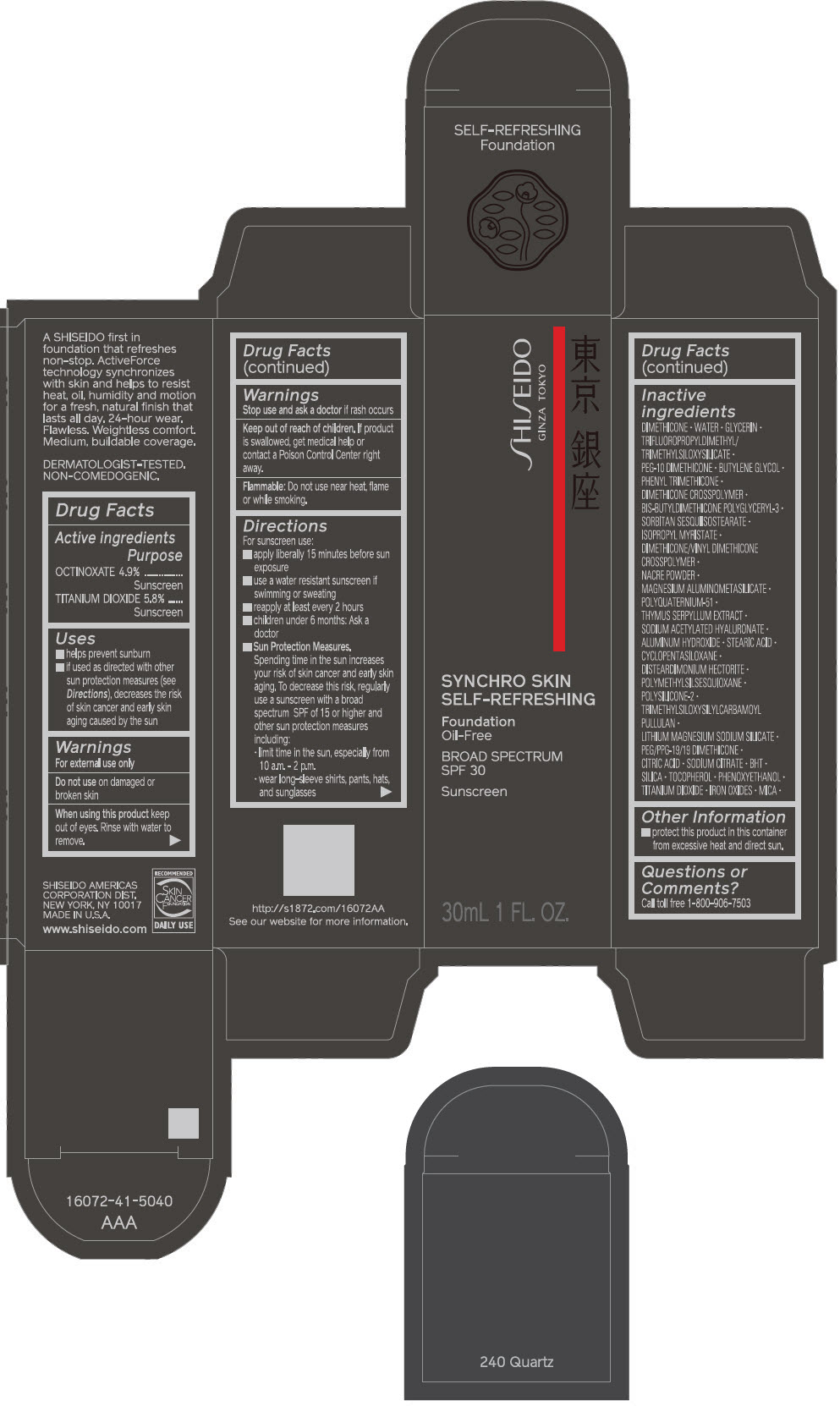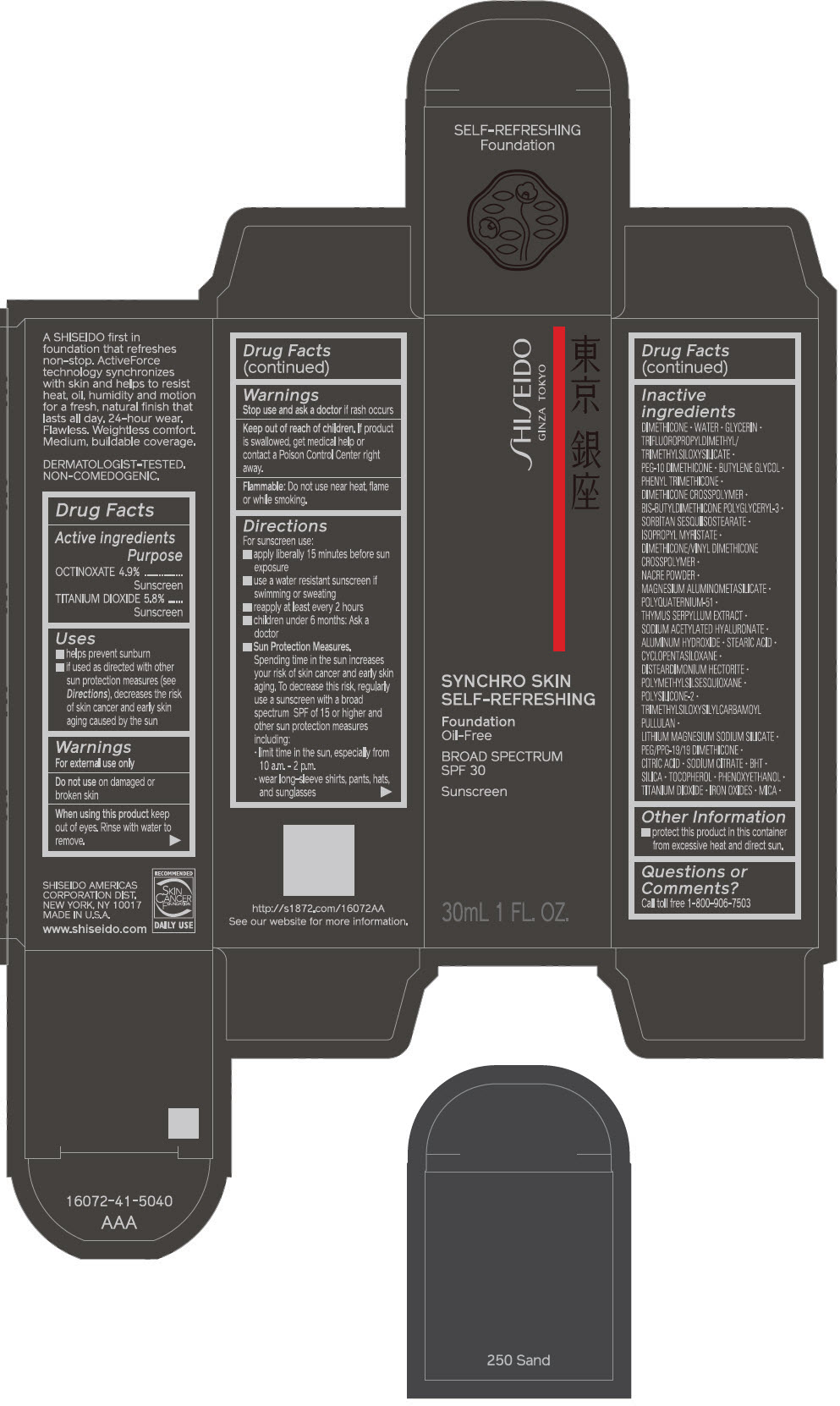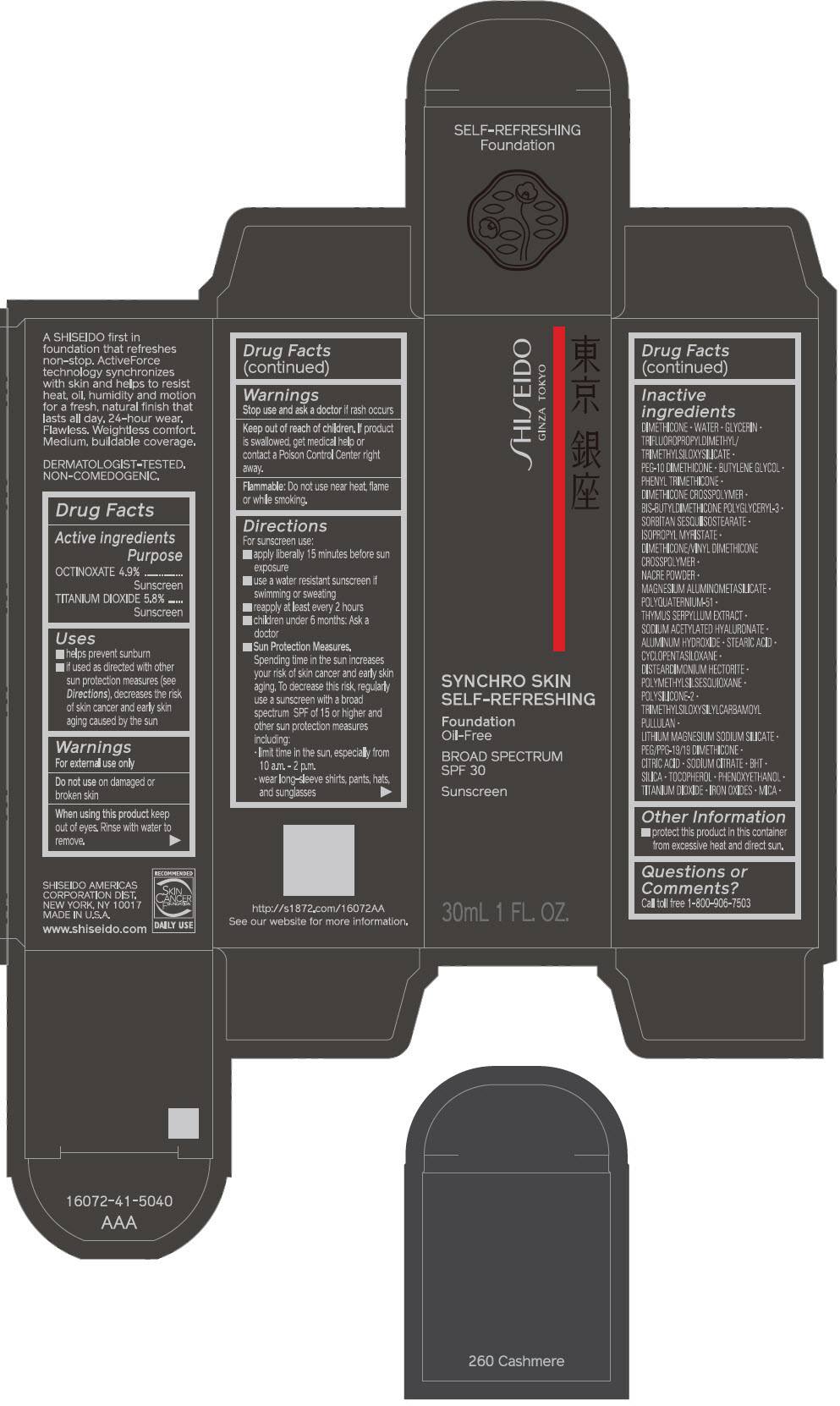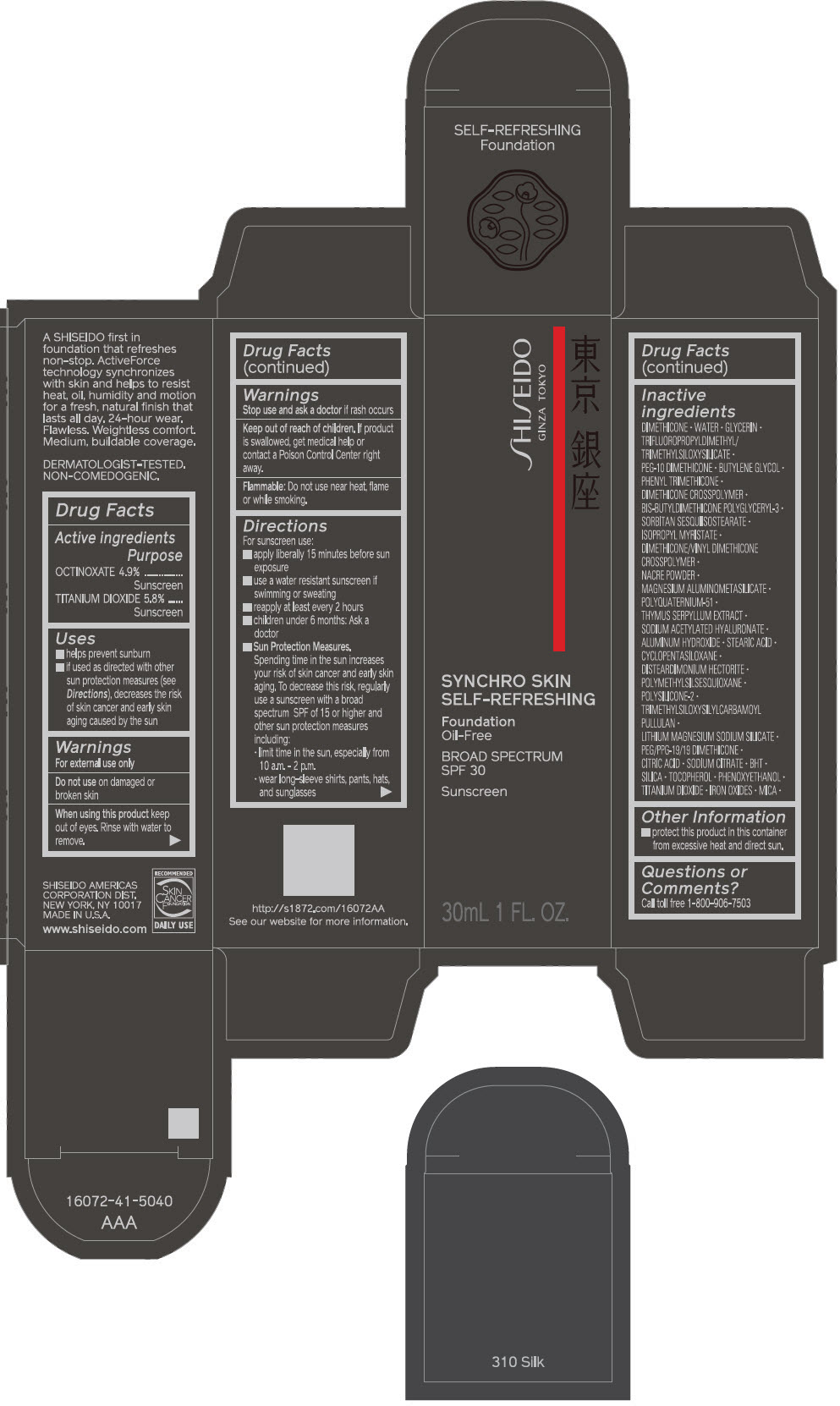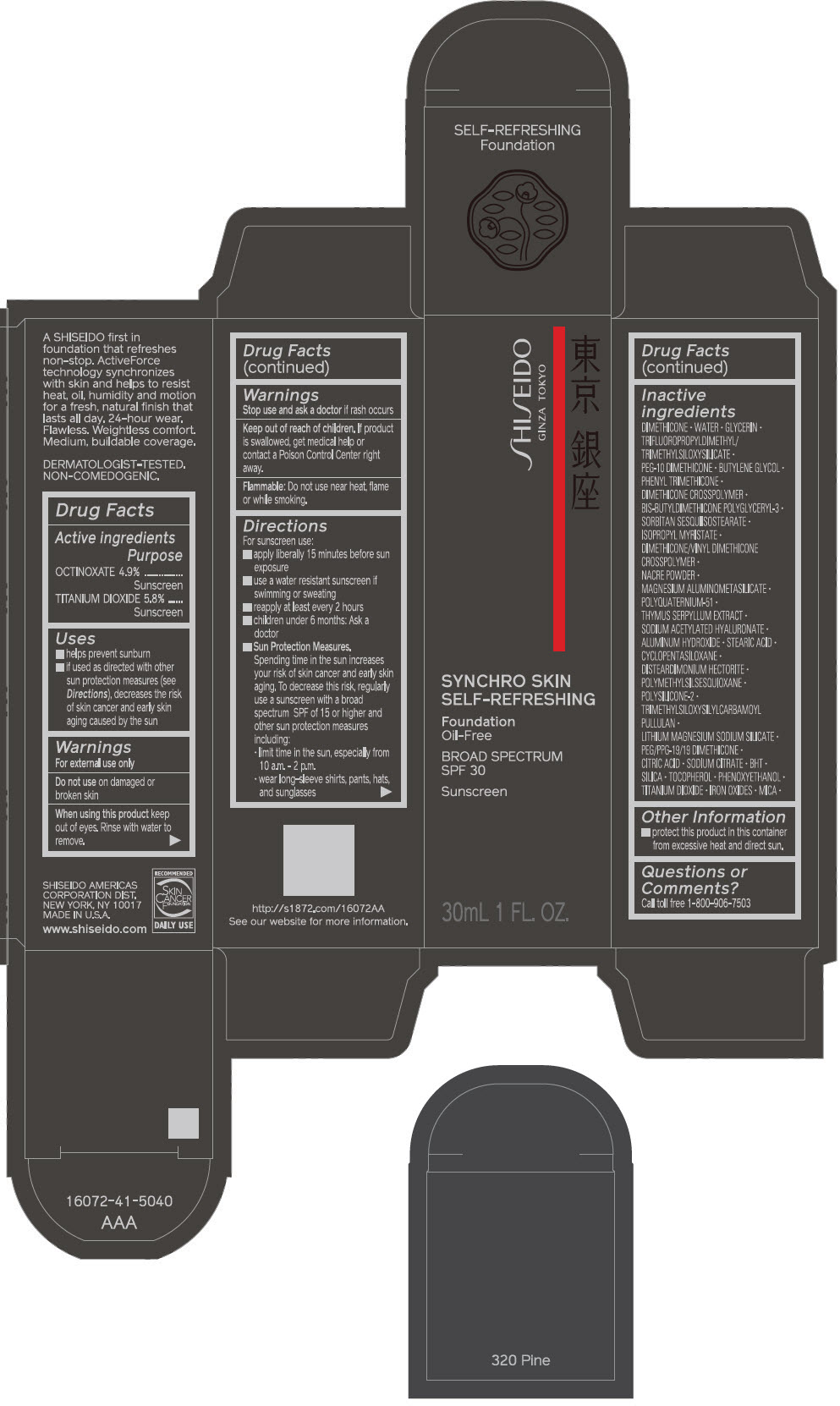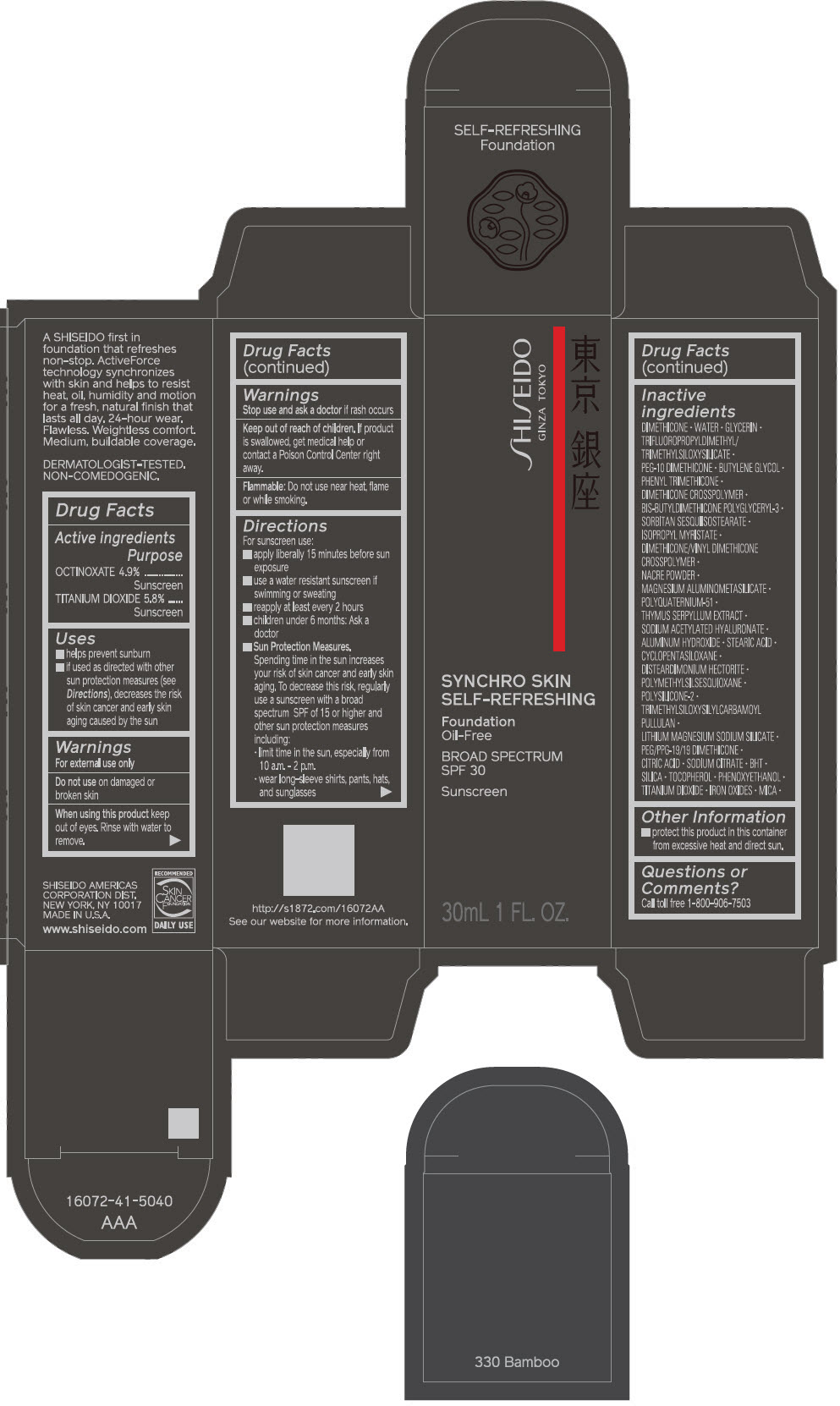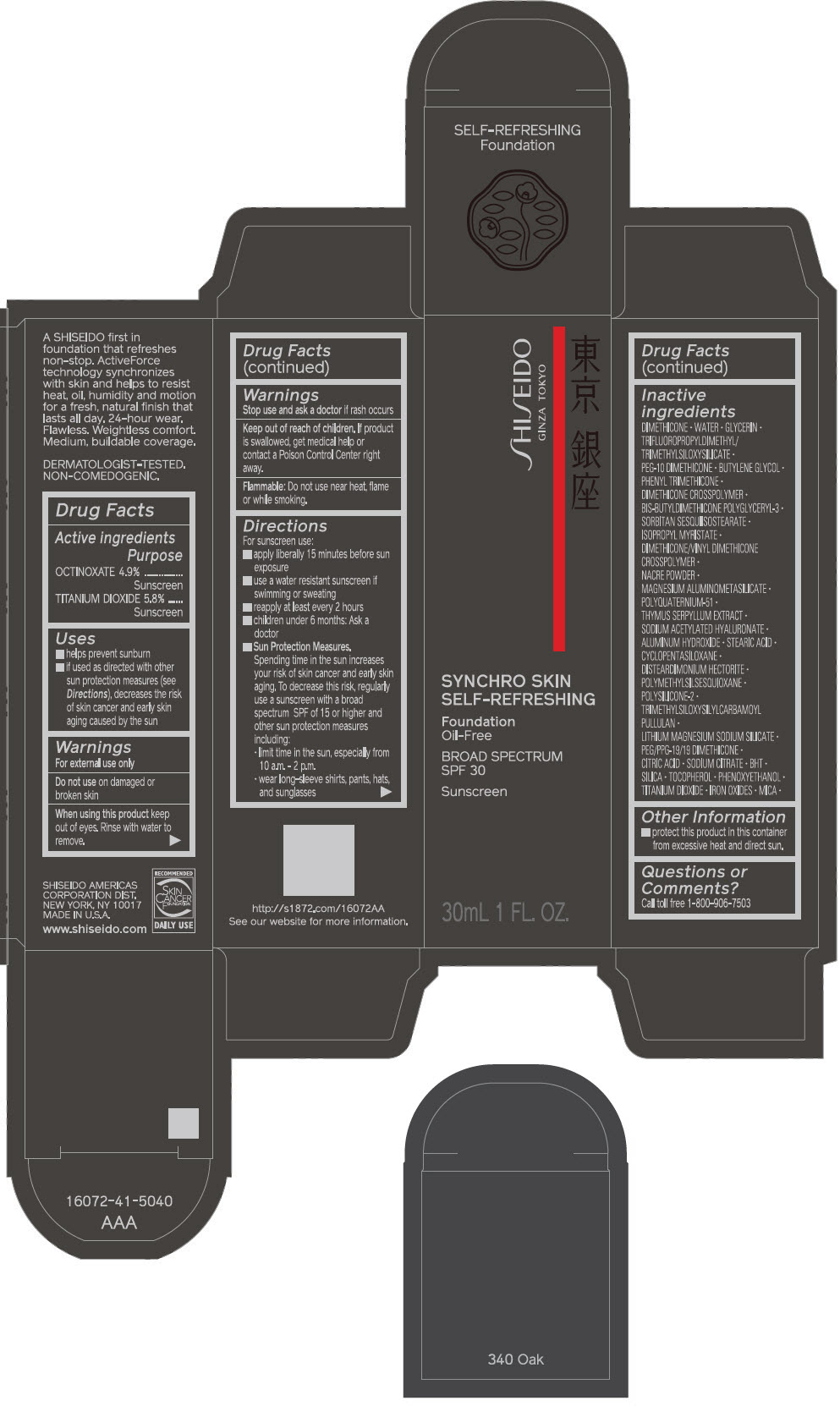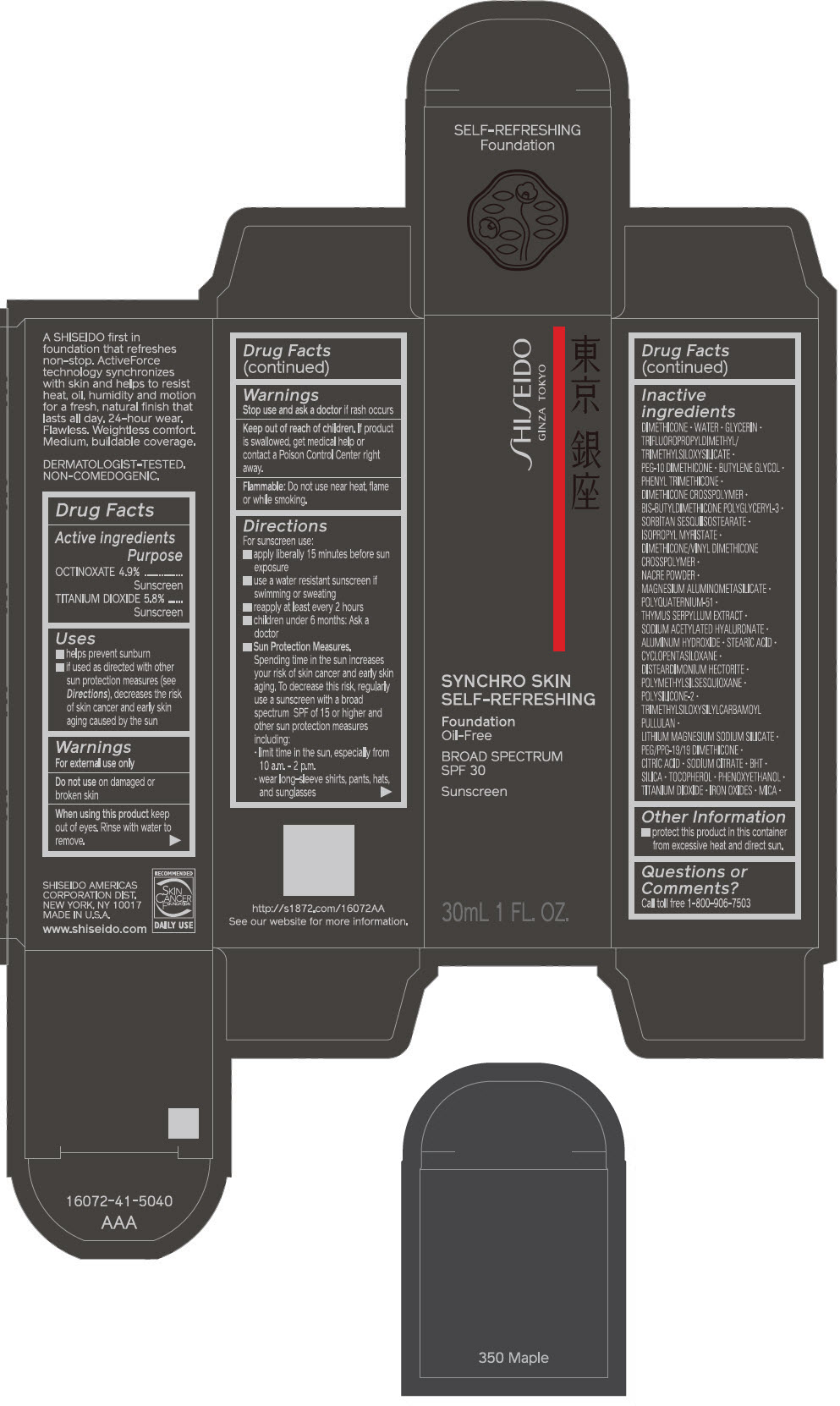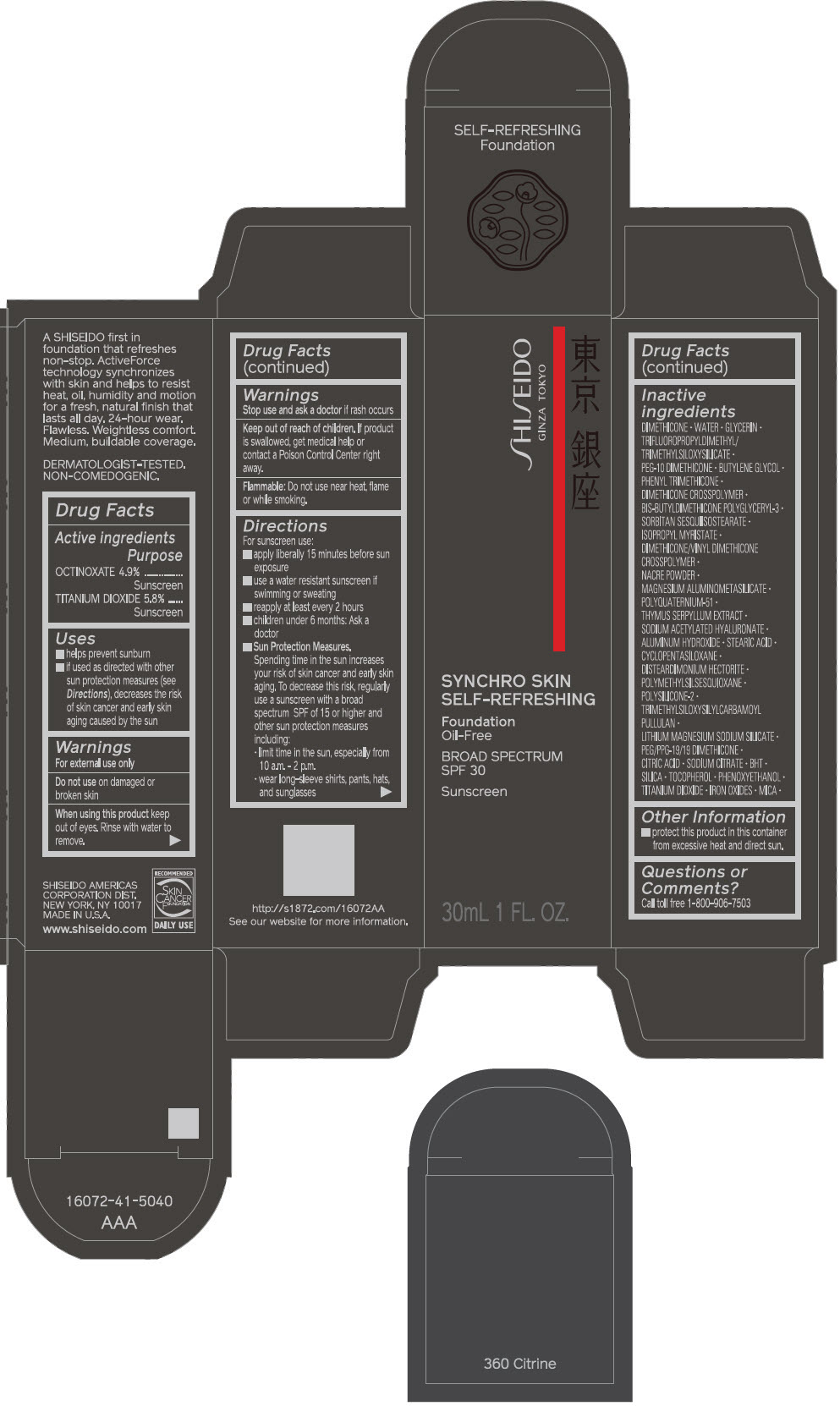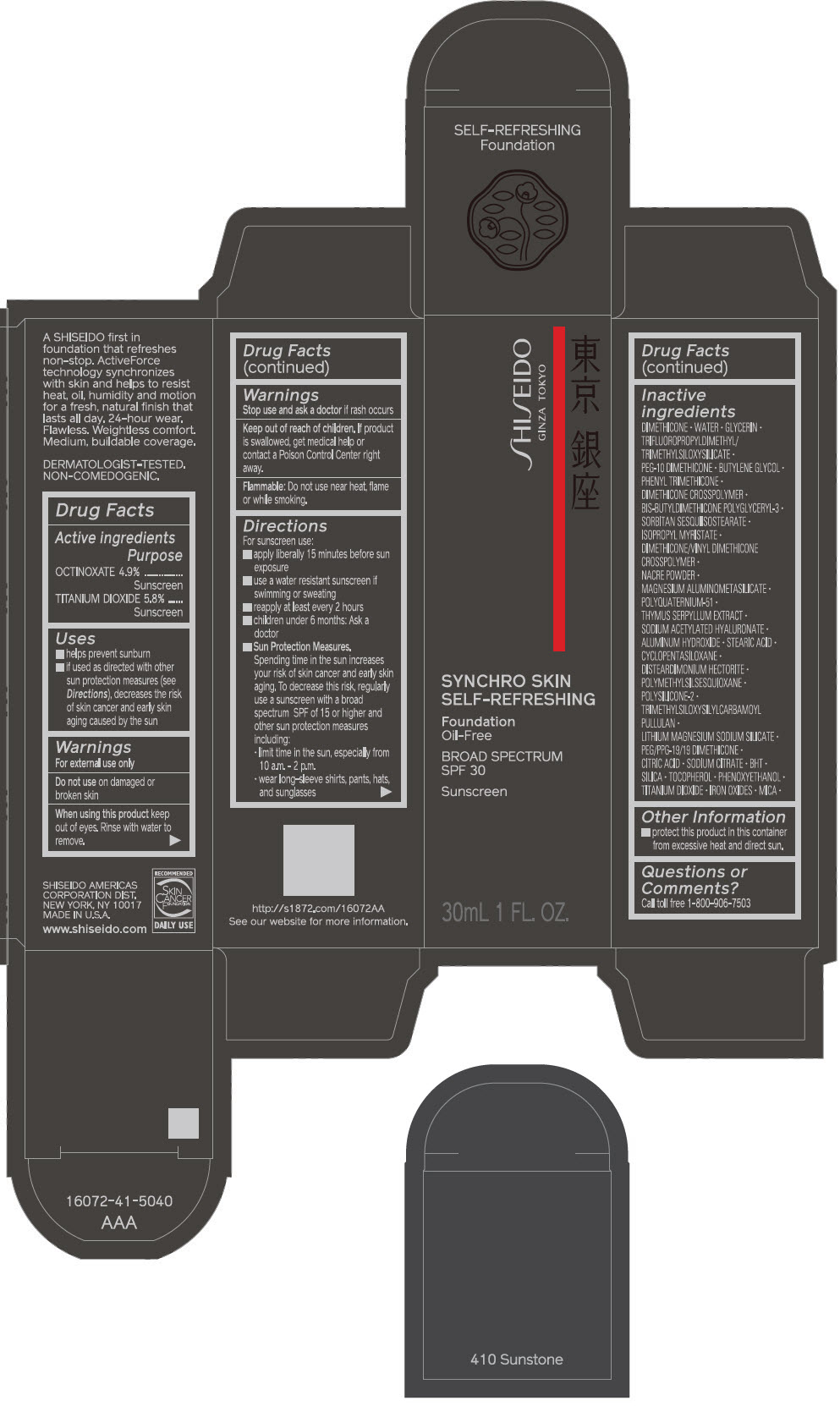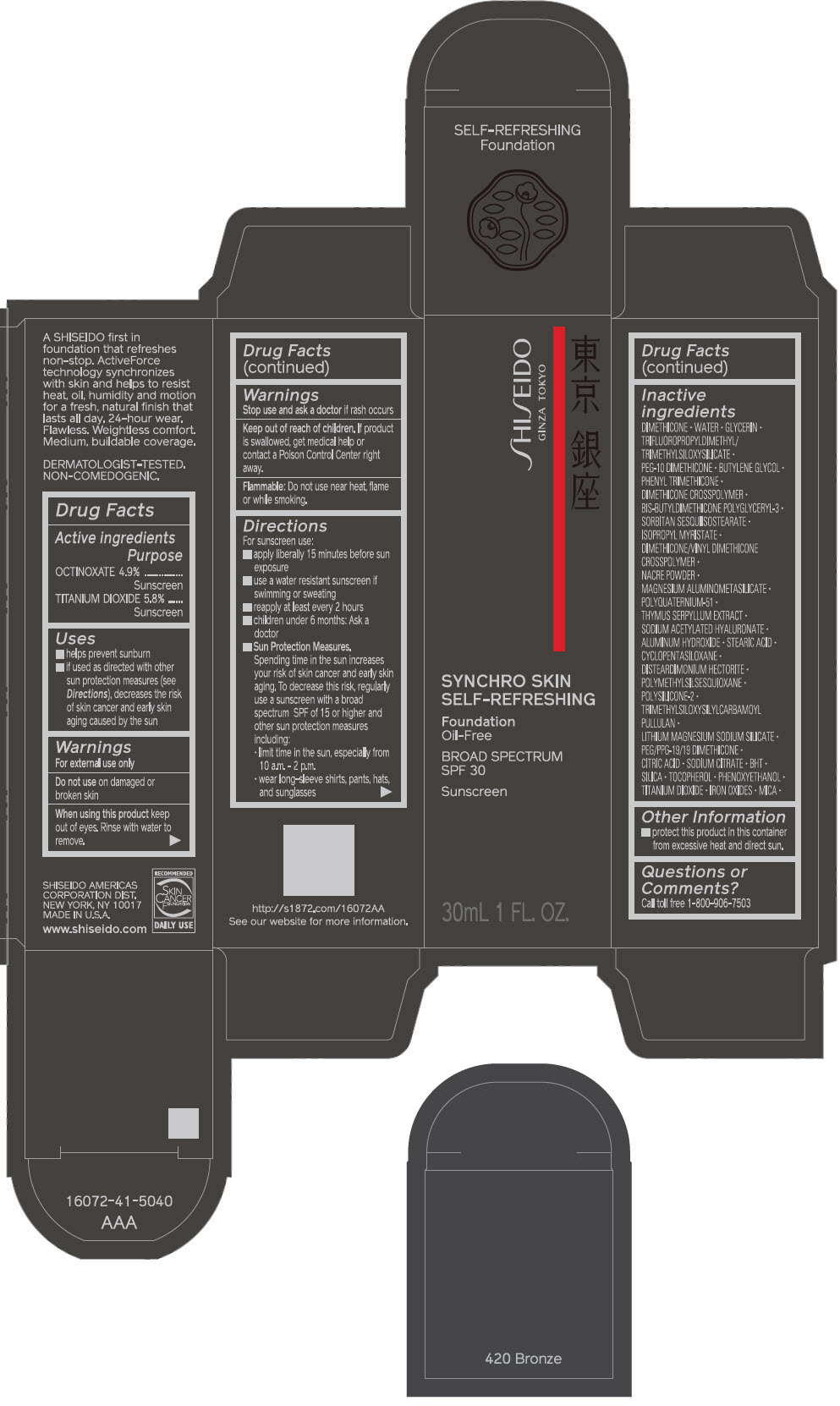 DRUG LABEL: SHISEIDO SYNCHRO SKIN SELF-REFRESHING FOUNDATION 110 ALABASTER
NDC: 58411-484 | Form: EMULSION
Manufacturer: SHISEIDO AMERICAS CORPORATION
Category: otc | Type: HUMAN OTC DRUG LABEL
Date: 20260105

ACTIVE INGREDIENTS: OCTINOXATE 1.69 g/30 mL; TITANIUM DIOXIDE 2.001 g/30 mL
INACTIVE INGREDIENTS: DIMETHICONE; WATER; GLYCERIN; PEG-10 DIMETHICONE (600 CST); BUTYLENE GLYCOL; PHENYL TRIMETHICONE; DIMETHICONE CROSSPOLYMER (450000 MPA.S AT 12% IN CYCLOPENTASILOXANE); SORBITAN SESQUIISOSTEARATE; ISOPROPYL MYRISTATE; DIMETHICONE/VINYL DIMETHICONE CROSSPOLYMER (SOFT PARTICLE); SILODRATE; POLYQUATERNIUM-51 (2-METHACRYLOYLOXYETHYL PHOSPHORYLCHOLINE/N-BUTYL METHACRYLATE; 3:7); THYMUS SERPYLLUM WHOLE; SODIUM ACETYLATED HYALURONATE; ALUMINUM HYDROXIDE; STEARIC ACID; CYCLOMETHICONE 5; DISTEARDIMONIUM HECTORITE; POLYMETHYLSILSESQUIOXANE (4.5 MICRONS); LAPONITE; PEG/PPG-19/19 DIMETHICONE; CITRIC ACID MONOHYDRATE; SODIUM CITRATE, UNSPECIFIED FORM; BUTYLATED HYDROXYTOLUENE; SILICON DIOXIDE; .ALPHA.-TOCOPHEROL; PHENOXYETHANOL; FERRIC OXIDE RED; FERRIC OXIDE YELLOW; FERROSOFERRIC OXIDE; MICA

SHISEIDO SYNCHRO SKIN SELF-REFRESHING FOUNDATION

Drug Facts

ACTIVE INGREDIENT

Active ingredients | Purpose
Octinoxate 4.9% | Sunscreen
Titanium Dioxide 5.8% | Sunscreen

Uses

- helps prevent sunburn
- if used as directed with other sun protection measures (see Directions), decreases the risk of skin cancer and early skin aging caused by the sun

Warnings

For external use only

Do not use on damaged or broken skin

WHEN USING

When using this productkeep out of eyes. Rinse with water to remove.

Stop use and ask a doctorif rash occurs.

Keep out of reach of children.If product is swallowed, get medical help or contact a Poison Control Center right away.

Directions

For sunscreen use:

- apply liberally 15 minutes before sun exposure
- use a water resistant sunscreen if swimming or sweating
- reapply at least every 2 hours
- children under 6 months: ask a doctor
- Sun Protection Measures. Spending time in the sun increases your risk of skin cancer and early skin aging. To decrease this risk, regularly use a sunscreen with a broad spectrum SPF of 15 or higher and other sun protection measures including:
  - limit time in the sun, especially from 10 a.m. – 2 p.m.
  - wear long-sleeve shirts, pants, hats, and sunglasses

Inactive Ingredients

DIMETHICONE･WATER･GLYCERIN･TRIFLUOROPROPYLDIMETHYL/TRIMETHYLSILOXYSILICATE･PEG-10 DIMETHICONE･BUTYLENE GLYCOL･PHENYL TRIMETHICONE･DIMETHICONE CROSSPOLYMER･BIS-BUTYLDIMETHICONE POLYGLYCERYL-3･SORBITAN SESQUIISOSTEARATE･ISOPROPYL MYRISTATE･DIMETHICONE/VINYL DIMETHICONE CROSSPOLYMER･NACRE POWDER･MAGNESIUM ALUMINOMETASILICATE･POLYQUATERNIUM-51･THYMUS SERPYLLUM EXTRACT･SODIUM ACETYLATED HYALURONATE･ALUMINUM HYDROXIDE･STEARIC ACID･CYCLOPENTASILOXANE･DISTEARDIMONIUM HECTORITE･POLYMETHYLSILSESQUIOXANE･POLYSILICONE-2･TRIMETHYLSILOXYSILYLCARBAMOYL PULLULAN･LITHIUM MAGNESIUM SODIUM SILICATE･PEG/PPG-19/19 DIMETHICONE･CITRIC ACID･SODIUM CITRATE･BHT･SILICA･TOCOPHEROL･PHENOXYETHANOL･TITANIUM DIOXIDE･IRON OXIDES･MICA･

Other information

Protect this product in this container from excessive heat and direct sun.

Questions or comments?

Call toll free 1-800-906-7503

PRINCIPAL DISPLAY PANEL - 30 mL Bottle Carton - 110 Alabaster

SHISEIDO
GINZA TOKYO

SYNCHRO SKIN
SELF-REFRESHING

Foundation
Oil-Free

BROAD SPECTRUM
SPF 30

Sunscreen

30mL 1 FL. OZ.

PRINCIPAL DISPLAY PANEL - 30 mL Bottle Carton - 120 Ivory

SHISEIDO
GINZA TOKYO

SYNCHRO SKIN
SELF-REFRESHING

Foundation
Oil-Free

BROAD SPECTRUM
SPF 30

Sunscreen

30mL 1 FL. OZ.

PRINCIPAL DISPLAY PANEL - 30 mL Bottle Carton - 130 Opal

SHISEIDO
GINZA TOKYO

SYNCHRO SKIN
SELF-REFRESHING

Foundation
Oil-Free

BROAD SPECTRUM
SPF 30

Sunscreen

30mL 1 FL. OZ.

PRINCIPAL DISPLAY PANEL - 30 mL Bottle Carton - 140 Porcelain

SHISEIDO
GINZA TOKYO

SYNCHRO SKIN
SELF-REFRESHING

Foundation
Oil-Free

BROAD SPECTRUM
SPF 30

Sunscreen

30mL 1 FL. OZ.

PRINCIPAL DISPLAY PANEL - 30 mL Bottle Carton - 150 Lace

SHISEIDO
GINZA TOKYO

SYNCHRO SKIN
SELF-REFRESHING

Foundation
Oil-Free

BROAD SPECTRUM
SPF 30

Sunscreen

30mL 1 FL. OZ.

PRINCIPAL DISPLAY PANEL - 30 mL Bottle Carton - 160 Shell

SHISEIDO
GINZA TOKYO

SYNCHRO SKIN
SELF-REFRESHING

Foundation
Oil-Free

BROAD SPECTRUM
SPF 30

Sunscreen

30mL 1 FL. OZ.

PRINCIPAL DISPLAY PANEL - 30 mL Bottle Carton - 210 Birch

SHISEIDO
GINZA TOKYO

SYNCHRO SKIN
SELF-REFRESHING

Foundation
Oil-Free

BROAD SPECTRUM
SPF 30

Sunscreen

30mL 1 FL. OZ.

PRINCIPAL DISPLAY PANEL - 30 mL Bottle Carton - 220 Linen

SHISEIDO
GINZA TOKYO

SYNCHRO SKIN
SELF-REFRESHING

Foundation
Oil-Free

BROAD SPECTRUM
SPF 30

Sunscreen

30mL 1 FL. OZ.

PRINCIPAL DISPLAY PANEL - 30 mL Bottle Carton - 230 Alder

SHISEIDO
GINZA TOKYO

SYNCHRO SKIN
SELF-REFRESHING

Foundation
Oil-Free

BROAD SPECTRUM
SPF 30

Sunscreen

30mL 1 FL. OZ.

PRINCIPAL DISPLAY PANEL - 30 mL Bottle Carton - 240 Quartz

SHISEIDO
GINZA TOKYO

SYNCHRO SKIN
SELF-REFRESHING

Foundation
Oil-Free

BROAD SPECTRUM
SPF 30

Sunscreen

30mL 1 FL. OZ.

PRINCIPAL DISPLAY PANEL - 30 mL Bottle Carton - 250 Sand

SHISEIDO
GINZA TOKYO

SYNCHRO SKIN
SELF-REFRESHING

Foundation
Oil-Free

BROAD SPECTRUM
SPF 30

Sunscreen

30mL 1 FL. OZ.

PRINCIPAL DISPLAY PANEL - 30 mL Bottle Carton - 260 Cashmere

SHISEIDO
GINZA TOKYO

SYNCHRO SKIN
SELF-REFRESHING

Foundation
Oil-Free

BROAD SPECTRUM
SPF 30

Sunscreen

30mL 1 FL. OZ.

PRINCIPAL DISPLAY PANEL - 30 mL Bottle Carton - 310 Silk

SHISEIDO
GINZA TOKYO

SYNCHRO SKIN
SELF-REFRESHING

Foundation
Oil-Free

BROAD SPECTRUM
SPF 30

Sunscreen

30mL 1 FL. OZ.

PRINCIPAL DISPLAY PANEL - 30 mL Bottle Carton - 320 Pine

SHISEIDO
GINZA TOKYO

SYNCHRO SKIN
SELF-REFRESHING

Foundation
Oil-Free

BROAD SPECTRUM
SPF 30

Sunscreen

30mL 1 FL. OZ.

PRINCIPAL DISPLAY PANEL - 30 mL Bottle Carton - 330 Bamboo

SHISEIDO
GINZA TOKYO

SYNCHRO SKIN
SELF-REFRESHING

Foundation
Oil-Free

BROAD SPECTRUM
SPF 30

Sunscreen

30mL 1 FL. OZ.

PRINCIPAL DISPLAY PANEL - 30 mL Bottle Carton - 340 Oak

SHISEIDO
GINZA TOKYO

SYNCHRO SKIN
SELF-REFRESHING

Foundation
Oil-Free

BROAD SPECTRUM
SPF 30

Sunscreen

30mL 1 FL. OZ.

PRINCIPAL DISPLAY PANEL - 30 mL Bottle Carton - 350 Maple

SHISEIDO
GINZA TOKYO

SYNCHRO SKIN
SELF-REFRESHING

Foundation
Oil-Free

BROAD SPECTRUM
SPF 30

Sunscreen

30mL 1 FL. OZ.

PRINCIPAL DISPLAY PANEL - 30 mL Bottle Carton - 360 Citrine

SHISEIDO
GINZA TOKYO

SYNCHRO SKIN
SELF-REFRESHING

Foundation
Oil-Free

BROAD SPECTRUM
SPF 30

Sunscreen

30mL 1 FL. OZ.

PRINCIPAL DISPLAY PANEL - 30 mL Bottle Carton - 410 Sunstone

SHISEIDO
GINZA TOKYO

SYNCHRO SKIN
SELF-REFRESHING

Foundation
Oil-Free

BROAD SPECTRUM
SPF 30

Sunscreen

30mL 1 FL. OZ.

PRINCIPAL DISPLAY PANEL - 30 mL Bottle Carton - 420 Bronze

SHISEIDO
GINZA TOKYO

SYNCHRO SKIN
SELF-REFRESHING

Foundation
Oil-Free

BROAD SPECTRUM
SPF 30

Sunscreen

30mL 1 FL. OZ.